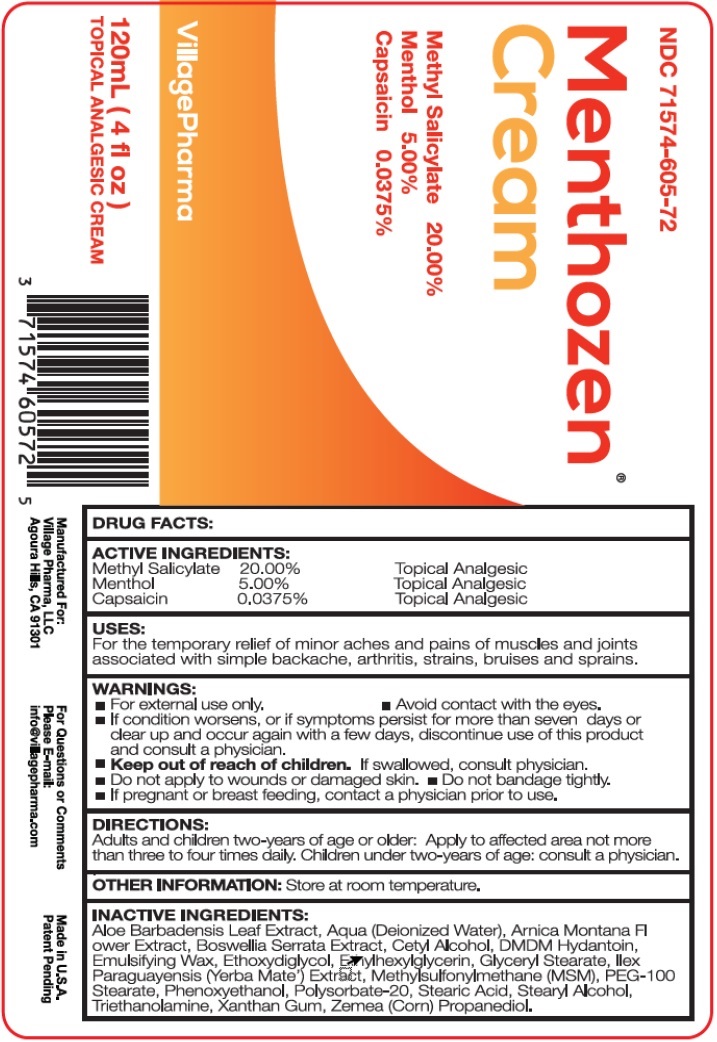 DRUG LABEL: Menthozen Cream
NDC: 71574-605 | Form: CREAM
Manufacturer: Village Pharma LLC
Category: otc | Type: HUMAN OTC DRUG LABEL
Date: 20260101

ACTIVE INGREDIENTS: METHYL SALICYLATE 200 mg/1 mL; MENTHOL, UNSPECIFIED FORM 50 mg/1 mL; CAPSAICIN 0.375 mg/1 mL
INACTIVE INGREDIENTS: ALOE VERA LEAF; WATER; ARNICA MONTANA WHOLE; INDIAN FRANKINCENSE; CETYL ALCOHOL; DMDM HYDANTOIN; DIETHYLENE GLYCOL MONOETHYL ETHER; ETHYLHEXYLGLYCERIN; GLYCERYL MONOSTEARATE; ILEX PARAGUARIENSIS LEAF; DIMETHYL SULFONE; PEG-100 MONOSTEARATE; PHENOXYETHANOL; POLYSORBATE 20; STEARIC ACID; STEARYL ALCOHOL; TROLAMINE; XANTHAN GUM; CORN

Menthozen Cream

ACTIVE INGREDIENTS:

Methyl Salicylate 20.00%

Menthol 5.00%

Capsaicin 0.0375%

PURPOSE

Topical Analgesic

USES:

For the temporary relief of minor aches and pains of muscles and joints associated with simple backache, arthritis, strains, bruises and sprains.

WARNINGS:

- For external use only.
- Avoid contact with the eyes.
- If condition worsens, or if symptoms persist for more than seven days or clear up and occur again with a few days, discontinue use of this product and consult a physician.

Keep out of reach of children.

- If swallowed, consult physician
- Do not apply to wounds or damaged skin.
- Do not bandage tightly.

If pregnant or breast feeding,

contact a physician prior to use.

DIRECTIONS

Adults and children two-years of age or older: Apply to affected area not more than three to four times daily. Children under two-years of age: consult a physician.

OTHER INFORMATION:

Store at room temperature.

INACTIVE INGREDIENTS

Aloe Barbadensis Leaf Extract, Aqua (Deionized Water), Arnica Montana Flower Extract, Boswellia Serrata Extract, Cetyl Alcohol, DMDM Hydantoin, Emulsifying Wax, Ethoxydiglycol, Ethylhexylglycerin, Glyceryl Stearate, Ilex Paraguariensis (Yerba Mate) Extract, Methylsulfonylmethane (MSM), PEG-100 Stearate, Phenoxyethanol, Polysorbate-20, Stearic Acid, Stearyl Alcohol, Triethanolamine, Xanthan Gum, Zemea (Corn) Propanediol.